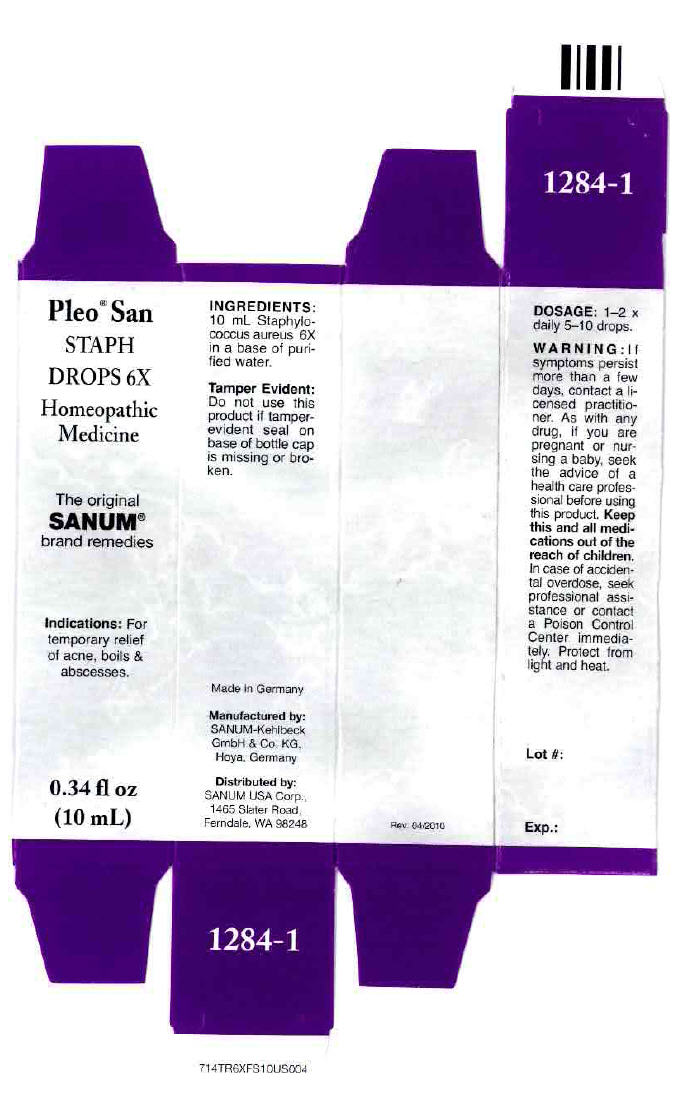 DRUG LABEL: Pleo San Staph
NDC: 60681-1284 | Form: SOLUTION/ DROPS
Manufacturer: Sanum Kehlbeck GmbH & Co. KG
Category: homeopathic | Type: HUMAN OTC DRUG LABEL
Date: 20111111

ACTIVE INGREDIENTS: staphylococcus aureus 6 [hp_X]/10 mL
INACTIVE INGREDIENTS: water

Pleo® San
STAPH
DROPS 6X

PURPOSE

Homeopathic Medicine

0.34 fl oz
(10 mL)

Indications

For temporary relief of acne, boils & abscesses.

INGREDIENTS

INACTIVE INGREDIENT

10 mL Staphylococcus aureus 6X in a base of purified water.

Tamper Evident

Do not use this product if tamper-evident seal on base of bottle cap is missing or broken.

DOSAGE

1–2 × daily 5–10 drops.

WARNING

If symptoms persist more than a few days, contact a licensed practitioner. As with any drug, if you are pregnant or nursing a baby, seek the advice of a health care professional before using this product.

KEEP OUT OF REACH OF CHILDREN

Keep this and all medications out of the reach of children. In case of accidental overdose, seek professional assistance or contact a Poison Control Center immediately.

STORAGE AND HANDLING

Protect from light and heat.

Made in Germany

Manufactured by:
SANUM-Kehlbeck
GmbH & Co. KG,
Hoya, Germany

Distributed by:
SANUM USA Corp.,
1465 Slater Road,
Ferndale, WA 98248

Rev. 04/2010

PRINCIPAL DISPLAY PANEL - 10 mL Bottle Carton

Pleo® San
STAPH
DROPS 6X

Homeopathic
Medicine

The original
SANUM®
brand remedies

Indications: For
temporary relief
of acne, boils &
abscesses.

0.34 fl oz
(10 mL)